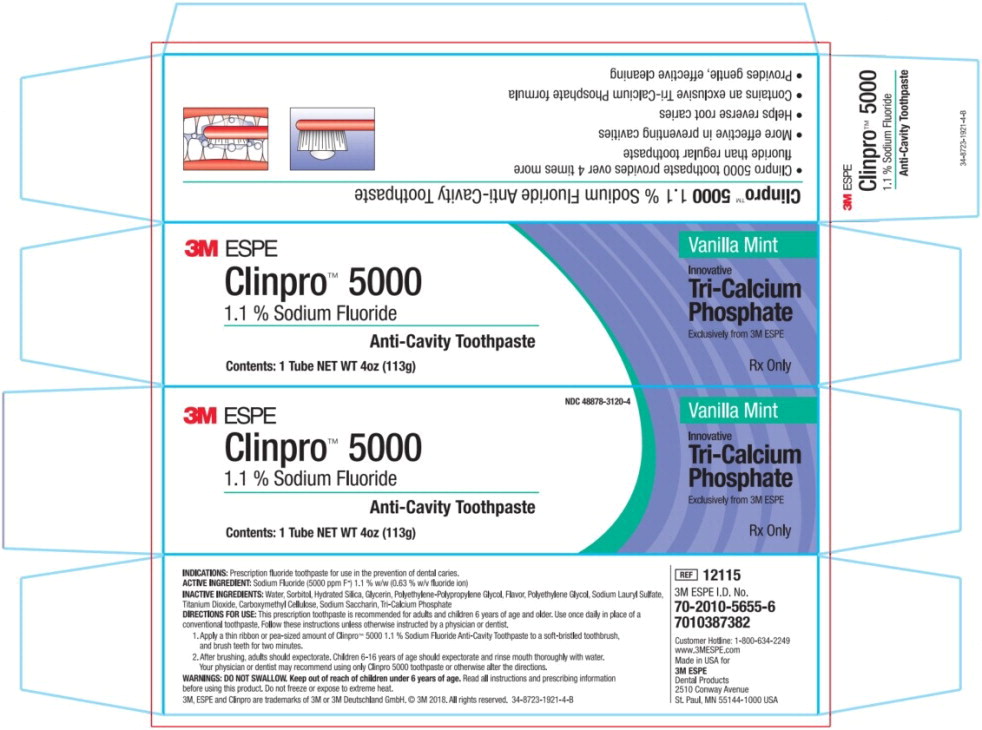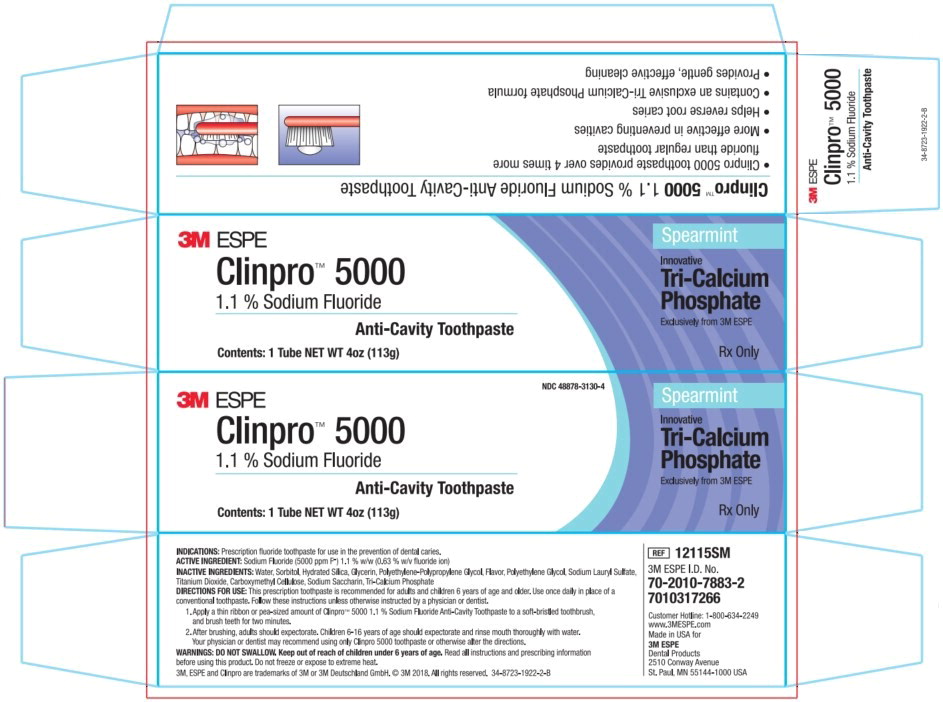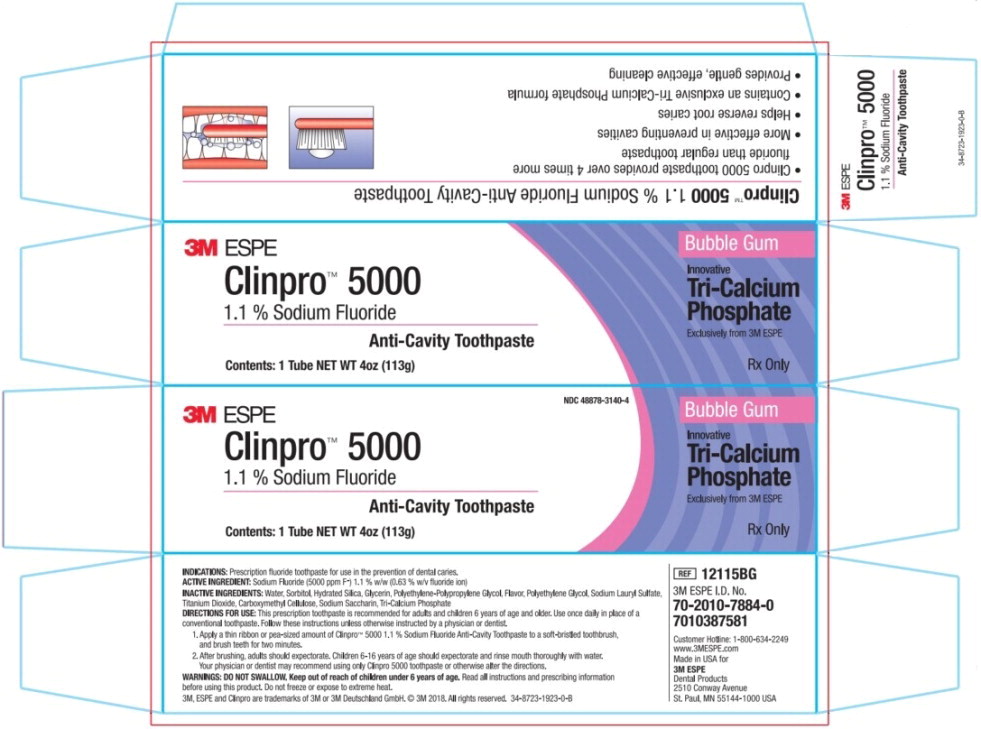 DRUG LABEL: Clinpro 5000
NDC: 48878-3120 | Form: PASTE, DENTIFRICE
Manufacturer: Solventum US LLC
Category: prescription | Type: HUMAN PRESCRIPTION DRUG LABEL
Date: 20240801

ACTIVE INGREDIENTS: sodium fluoride 5 mg/1 g
INACTIVE INGREDIENTS: Water; Sorbitol; Silicon Dioxide; Glycerin; Polyethylene Glycol, Unspecified; Sodium Lauryl Sulfate; Titanium Dioxide; Carboxymethylcellulose Sodium; Saccharin Sodium; Tricalcium Phosphate

HIGHLIGHTS OF PRESCRIBING INFORMATION

These highlights do not include all the information needed to use 3MTM ESPETM ClinproTM 5000 Anti-Cavity Toothpaste safely and effectively. See full prescribing information for Clinpro 5000 Anti-Cavity Toothpaste.
3MTM ESPETM Clinpro 5000 1.1% Sodium Fluoride Anti-Cavity Toothpaste for oral use.
Initial U.S. Approval: None

1 INDICATIONS AND USAGE

Clinpro 5000 Anti-Cavity Toothpaste is indicated for use as part of a professional program for the prevention and control of dental caries. (1)

2 DOSAGE AND ADMINISTRATION

- Use once daily in place of conventional toothpaste unless instructed otherwise by a physician or dentist. (2)
- Apply a thin ribbon or pea-sized amount of Clinpro 5000 Anti-Cavity Toothpaste using a soft-bristled toothbrush and brush teeth for at least two minutes. (2)
- After brushing adults should expectorate. Children 6 to 16 years of age should expectorate and rinse mouth thoroughly with water. (2)

3 DOSAGE FORMS AND STRENGTHS

White toothpaste containing 1.1% sodium fluoride (3)

4 CONTRAINDICATIONS

Do not use in children under 6 years of age unless recommended by a dentist or physician. (4)

5 WARNINGS AND PRECAUTIONS

- Do not swallow. (5)
- Keep out of reach of children under 6 years of age. (5)
- Repeated ingestion of high levels of fluoride may cause dental fluorosis. (5)

6 ADVERSE REACTIONS

Allergic reactions and other idiosyncrasies have been rarely reported. (6)

To report SUSPECTED ADVERSE REACTIONS, contact 3M ESPE Dental Products Division at 1-800-634-2249 or www.3MESPE.com, or FDA at 1-800-FDA-1088 or www.fda.gov/medwatch

FULL PRESCRIBING INFORMATION

1 INDICATIONS AND USAGE

Clinpro 5000 Anti-Cavity Toothpaste is indicated for use as part of a professional program for the prevention and control of dental caries.

2 DOSAGE AND ADMINISTRATION

• Use once daily in place of conventional toothpaste unless instructed otherwise by a physician or dentist.

• Apply a thin ribbon or pea-sized amount of Clinpro 5000 Anti-Cavity Toothpaste using a soft-bristled toothbrush and brush teeth for at least two minutes.

• After brushing adults should expectorate. Children 6 to 16 years of age should expectorate and rinse mouth thoroughly with water.

• Follow these instructions or use as directed by a dental professional.

3 DOSAGE FORMS AND STRENGTHS

White toothpaste containing 1.1% sodium fluoride

4 CONTRAINDICATIONS

Do not use in children under 6 years of age unless recommended by a dentist or physician.

5 WARNINGS AND PRECAUTIONS

• DO NOT SWALLOW. If more than a pea-sized amount of Clinpro 5000 Anti-Cavity Toothpaste is swallowed, contact a medical or dental professional or a poison control center.

• Keep out of reach of children under 6 years of age.

• Repeated ingestion of high levels of fluoride may cause dental fluorosis. For this reason, use in children with developing dentition requires special supervision to prevent swallowing. Prescribing dentists and physicians should consider risk of fluorosis when prescribing for use in children less than 6 years of age.

6 ADVERSE REACTIONS

Allergic reactions and other idiosyncrasies have been rarely reported.

8 USE IN SPECIFIC POPULATIONS

8.1 Pregnancy

Fluoride crosses the placenta in women and has been measured in cord blood, amniotic fluid, and serum of newborn children, but without a consistent correlation to maternal serum fluoride levels.^1,2 There are no data to indicate an increased susceptibility to fluorosis during pregnancy. Developmental studies were conducted by the National Toxicology Program, with sodium fluoride administered in the drinking water to pregnant rats and rabbits. No developmental toxicity was observed, even at doses that caused maternal toxicity. The No Adverse Effect Levels were about 29 mg/kg-day and 27 mg/kg-day for rabbits and rats, respectively.^3 There is no conclusive evidence of fluoride developmental effects in humans.^1,2

The Institute of Medicine established a fluoride Upper Limit of 10 mg/day for pregnant women.^2

Prescribing physicians and dentists should consider total fluoride exposure (dental care plus food, water and other sources) when prescribing the product for use in pregnant women or women who may become pregnant.

8.3 Nursing Mothers

An extremely small proportion of fluoride in drinking water is transferred to breast milk. The Institute of Medicine established a fluoride Upper Limit of 10 mg/day for nursing women.^2 Prescribing physicians and dentists should consider total fluoride exposure (dental care plus food, water and other sources) when prescribing the product for use in women who are nursing.

8.4 Pediatric Use

The primary adverse effects of fluoride are fluorosis of dental enamel and of the skeleton; these effects occur at exposures below those associated with other adverse health effects. The population most at risk for dental fluorosis is children during the period of tooth formation, i.e. from birth to 8 years of age. For this population, the Institute of Medicine established Fluoride Upper Limits of intake based on the risk of dental fluorosis. In populations with permanent dentition, skeletal fluorosis is the greatest risk from excessive fluoride. For this population the Institute of Medicine (IOM) established Fluoride Upper Limits based on the risk of skeletal fluorosis.^2

Population | IOM Fluoride Upper Limit
Infants 0-6 months old | 0.7 mg/day
Infants 7-12 months old | 0.9 mg/day
Children 1-3 years old | 1.3 mg/day
Children 4-8 years old | 2.2 mg/day
Children > 8 years old | 10 mg/day

Prescribing physicians and dentists should consider total fluoride exposure (dental care plus food, water and other sources) when prescribing the product for use in children.

8.5 Geriatric Use

No studies of Clinpro 5000 Anti-Cavity Toothpaste have been conducted to determine whether subjects aged 65 and over respond differently from younger subjects.

10 OVERDOSAGE

Ingestion of large amounts of fluoride may result in abdominal pain, stomach upset, nausea, vomiting, and diarrhea. These symptoms may occur at overdosages of 5 mg/kg of body weight. Fluoride doses of 16 mg/kg have been fatal.

Treatment Recommendations for Overdose of Clinpro 5000 Anti-Cavity Toothpaste^4
Ingested fluoride dose | Amount for 10 kg (22 pound) child* | Recommended action to take
Less than 5 mg/kg | This equals less than ½ ounce (or less than 3 teaspoons). | Do not induce vomiting. Give 1-2 glasses of milk and observe for symptoms of stomach upset. If symptoms persist more than a few hours, seek medical attention or contact a poison control center.
5 mg/kg or more | This equals about ½ ounce (about 1 tablespoon) or more. | Do not induce vomiting. Give 1-2 glasses of milk and seek medical attention or contact a poison control center.
15 mg/kg | This equals 1 ounce or ¼ of the tube. | Seek immediate medical attention. Do not induce vomiting. Give 1-2 glasses of milk.
*The amount to reach the fluoride dose will be proportionately larger with older children and adults.
A thin ribbon or pea-sized amount of Clinpro 5000 Anti-Cavity Toothpaste weighs approximately 0.3 g and contains approximately 1.5 mg of fluoride ion. A 4 oz. tube contains 564 mg of fluoride ion.

11 DESCRIPTION

Clinpro 5000 1.1% Sodium Fluoride Anti-Cavity Toothpaste is a self-applied fluoride dentifrice for the prevention of dental caries. Each gram contains 5 mg of fluoride ion in a neutral pH base, consisting of water, sorbitol, hydrated silica, glycerin, polyethylene-polypropylene glycol, flavor, polyethylene glycol, sodium lauryl sulfate, titanium dioxide, carboxymethyl cellulose, sodium saccharin and tri-calcium phosphate.

12 CLINICAL PHARMACOLOGY

Clinpro 5000 1.1% Sodium Fluoride Anti-Cavity Toothpaste aids in the prevention of tooth decay. Fluoride delivered from Clinpro 5000 inhibits the demineralization of sound teeth and enhances the remineralization (i.e., repair) of demineralized teeth. During tooth brushing, fluoride is taken up by teeth and dental plaque. Fluoride is taken up with calcium and phosphate by demineralized teeth resulting in an improved tooth structure than contains more fluoride and less carbonate than naturally occurring tooth structure and is more resistant to acid challenge. Additionally, calcium fluoride is formed on the crystal structure of teeth. As the pH of the mouth drops, fluoride is released from calcium fluoride and aids in the remineralization of teeth. Fluoride taken up into plaque alters the activity of cariogenic bacteria. Fluoride inhibits the process by which cariogenic bacteria metabolize carbohydrates resulting in less acid and adhesive polysaccharide production by the bacteria.

15 REFERENCES

1. National Research Council. Fluoride in drinking water: A scientific review of EPA's standards; National Academies Press 2006.
2. IOM. Dietary Reference Intakes: The essential guide to nutrient requirements. National Academies Press 2006.
3. Heindel JJ, et al. Developmental toxicity evaluation of sodium fluoride administered to rats and rabbits in drinking water. Fundam Appl Toxicol 1996;30(2):162-177.
4. Poisindex. Toxicologic Management – Fluoride. Thomson Micromedex.

16 HOW SUPPLIED/STORAGE AND HANDLING

Clinpro 5000 Anti-Cavity Toothpaste is supplied as a white dentifrice paste in a 4 oz. (113 gm) plastic tube (NDC 48878-3120-4, Vanilla Mint Flavor; NDC 48878-3130-4 Spearmint Flavor; NDC 48878-3140-4 Bubble Gum Flavor).

Storage

This product is designed to be stored and used at room temperature. Do not freeze or expose to extreme heat. See outer package for expiration date.

Manufactured for:
3M ESPE
Dental Products
2510 Conway Avenue
St. Paul, MN 55144-1000 USA
Revision date: 01/11/2012

Rx Only

3M, ESPE, and Clinpro are trademarks of 3M or 3M Deutschland GmbH.
© 3M 2016. All rights reserved.

Principal Display Panel – Box Label

3M ESPE

NDC 48878-3120-4

Clinpro™ 5000

Vanilla Mint

1.1% Sodium Fluoride

Anti-Cavity Toothpaste

Innovative

Tri-Calcium

Phosphate

Exclusively from 3M ESPE

Contents: 1 Tube NET WT 4oz (113g)

Rx Only

Principal Display Panel – Box Label

3M ESPE

NDC 48878-3130-4

Clinpro™ 5000

Spearmint

1.1% Sodium Fluoride

Anti-Cavity Toothpaste

Innovative

Tri-Calcium

Phosphate

Exclusively from 3M ESPE

Contents: 1 Tube NET WT 4oz (113g)

Rx Only

Principal Display Panel – Box Label

3M ESPE

NDC 48878-3140-4

Clinpro™ 5000

Bubble Gum

1.1% Sodium Fluoride

Anti-Cavity Toothpaste

Innovative

Tri-Calcium

Phosphate

Exclusively from 3M ESPE

Contents: 1 Tube NET WT 4oz (113g)

Rx Only